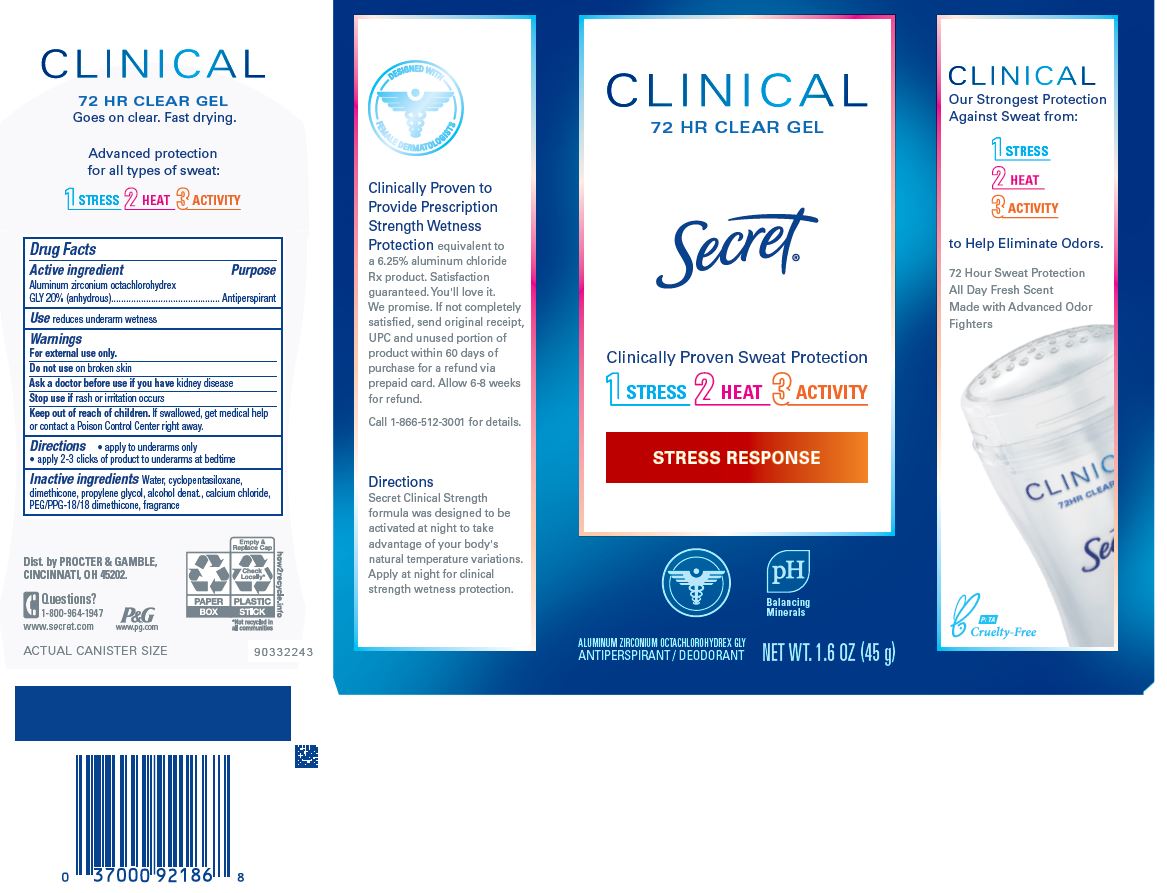 DRUG LABEL: Secret Clinical Strength Clear Stress Response
NDC: 69423-013 | Form: GEL
Manufacturer: The Procter & Gamble Manufacturing Company
Category: otc | Type: HUMAN OTC DRUG LABEL
Date: 20251218

ACTIVE INGREDIENTS: ALUMINUM ZIRCONIUM OCTACHLOROHYDREX GLY 20 g/100 g
INACTIVE INGREDIENTS: WATER; CYCLOPENTASILOXANE; DIMETHICONE; PROPYLENE GLYCOL; ALCOHOL; CALCIUM CHLORIDE; PEG/PPG-18/18 DIMETHICONE

Secret® Clinical Strength Clear Stress Response

Drug Facts

Active ingredient

Aluminum zirconium octachlorohydrex Gly 20% (anhydrous)

Purpose

Antiperspirant

Use

- reduces underarm wetness

Warnings

For external use only.

Do not use on broken skin

Ask a doctor before use if you have kidney disease

Stop use if rash or irritation occurs

Keep out of reach of children. If swallowed, get medical help or contact a Poison Control Center right away.

Directions

- apply to underarms only
- apply 2-3 clicks of product to underarms at bedtime

Inactive ingredients

water, cyclopentasiloxane, dimethicone, propylene glycol, alcohol denat., calcium chloride, PEG/PPG-18/18 dimethicone, fragrance

Questions?

1-800-964-1947

Dist. by PROCTER & GAMBLE,
CINCINNATI, OH 45202.

PRINCIPAL DISPLAY PANEL - 45 g Cylinder Carton

CLINICAL

72 HR CLEAR GEL

Secret ®
Clinically Proven Sweat Protection

1 STRESS 2 HEAT 3 ACtivity

STRESS RESPONSE

ALUMINUM ZIRCONIUM OCTACHLOROHYDREX GLY
ANTIPERSPIRANT

NET WT. 1.6 OZ (45 g)